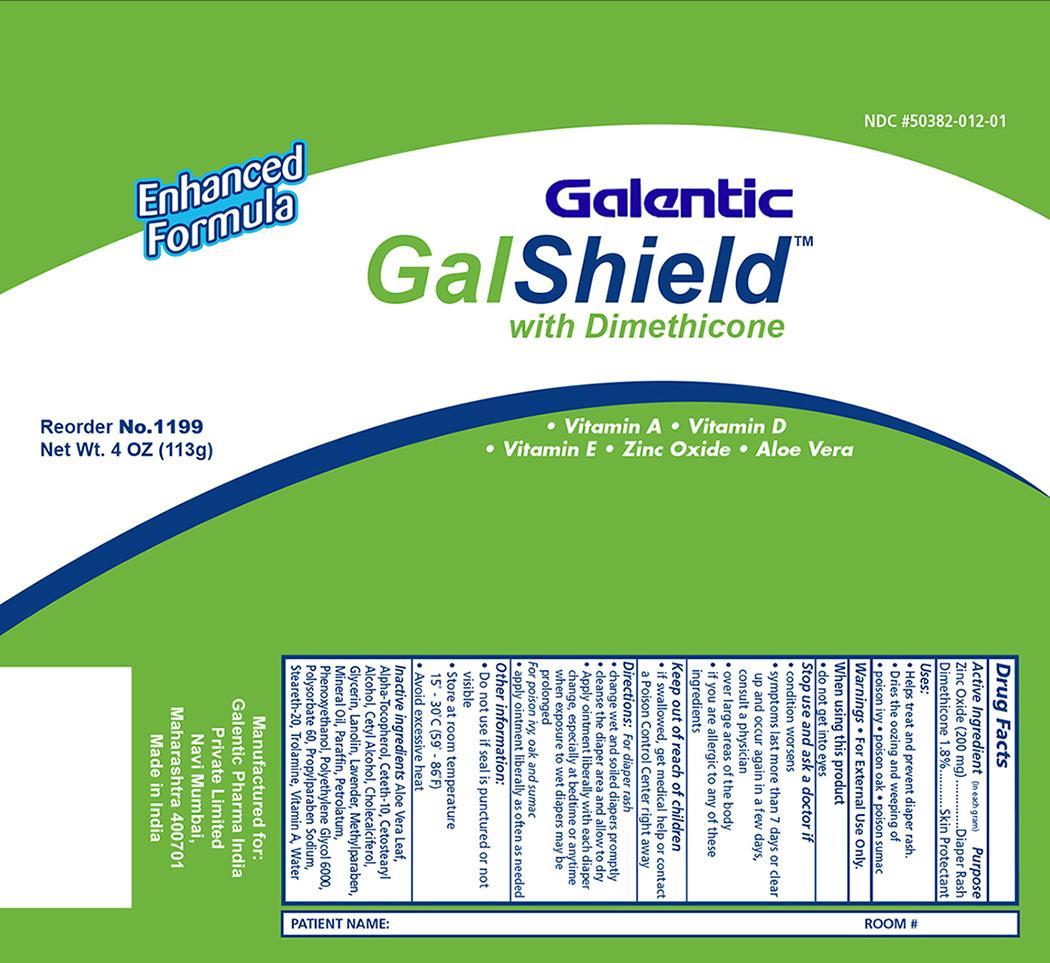 DRUG LABEL: Zinc Oxide and Dimethicone
NDC: 50382-012 | Form: CREAM
Manufacturer: Galentic Pharma (India) Private Limited
Category: otc | Type: HUMAN OTC DRUG LABEL
Date: 20130809

ACTIVE INGREDIENTS: ZINC OXIDE 200 mg/1 g; DIMETHICONE 18 mg/1 g
INACTIVE INGREDIENTS: ALOE VERA LEAF; CETYL ALCOHOL; CHOLECALCIFEROL; LANOLIN; METHYLPARABEN; MINERAL OIL; PETROLATUM; WATER; CETETH-10; PARAFFIN; PROPYLPARABEN SODIUM; GLYCERIN; PHENOXYETHANOL; STEARETH-20; POLYETHYLENE GLYCOL 6000; POLYSORBATE 60; CETOSTEARYL ALCOHOL; VITAMIN A; ALPHA-TOCOPHEROL; TROLAMINE

Galshield Zinc Oxide / Dimethicone

Active ingredient Purpose
Zinc Oxide (200 mg) Diaper Rash
Dimethicone 1.8% Skin Protectant

Purpose:

- Helps treat and prevent diaper rash.
- Dries the oozing and weeping of
- poison ivy
- poison oak
- poison sumac

Warnings:

For external use only

Dosage and Administration:

For diaper rash

- change wet and soiled diapers promptly
- cleanse the diaper area and allow to dry
- Apply ointment liberally with each diaper change, especially at bedtime or anytime when exposure to wet diapers may be prolonged

For poison ivy, oak and sumac

- apply ointment liberally as often as needed

Other information

- Do not use if seal is punctured or not visible
- store at room temperature 15°-30° C (59°-86° F)
- avoid excessive heat

Inactive ingredients

Aloe Barbadensis Leaf Juice, Cetyl Alcohol, Cholecaliferol, Diazolidinyl Urea, Fragrance, Lanolin, Methylparaben, Mineral Oil, Petrolatum, Purified Water, Retinyl Palmitate, Sodium Borate, Stearic Acid, Tocopheryl Acetate, Yellow 5, Yellow 6, Zea Mays (Corn) oil

Stop use if

- conditions worsen
- symptoms last more than 7 days or clear up and occur in a few days, consult a physician
- over large areas of the body
- if you are allergic to these ingredients

Indications and Usage

Indications are for diaper rash and general skin protectant.

Do not use

- deep or puncture wounds
- animal bites
- serious burns

Keep out of reach of children

- If swallowed, get medical help or contact a Poison Control Center right away.

Principal Display Panel

GalShield with Dimethicone

GalShield D.jpg